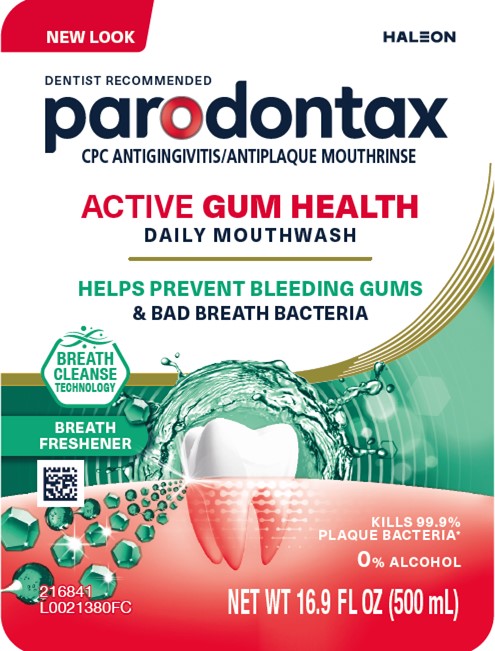 DRUG LABEL: Parodontax

NDC: 0135-0652 | Form: LIQUID
Manufacturer: Haleon US Holdings LLC
Category: otc | Type: HUMAN OTC DRUG LABEL
Date: 20250508

ACTIVE INGREDIENTS: CETYLPYRIDINIUM CHLORIDE 70 mg/1 mL
INACTIVE INGREDIENTS: GLYCERIN; POLOXAMER 407; BENZOIC ACID; SODIUM BENZOATE; SUCRALOSE; ZINC LACTATE; SACCHARIN SODIUM; FD&C GREEN NO. 3; FD&C YELLOW NO. 6; CINNAMALDEHYDE

Drug Facts

Active ingredient

Cetylpyridinium chloride 0.07% w/w

Purposes

Antigingivitis, Antiplaque

Uses

helps prevent and reduce plaque that leads to

■ gingivitis, an early form of gum disease

■ bleeding gums

Warnings

Stop use and ask a dentist if

■ irritation occurs

■ gingivitis, bleeding, or redness persists for more than 2 weeks

■ you have painful or swollen gums, pus from the gum line, loose teeth, or increasing spacing between the teeth. These may be signs or symptoms of periodontitis, a serious form of gum disease.

Keep out of reach of children under 6 years of age.

If more than used for rinsing is accidentally swallowed, get medical help or contact a Poison Control Center right away.

Directions(500 mL)

■ adults and children 6 years of age and older:Vigorously swish 20 milliliters of the rinse between your teeth twice a day for 30 seconds and then spit out. Do not swallow the rinse. Do not rinse with water. Do not drink from the bottle.

■ children 6 years to under 12 years of age:supervise use

■ children under 6 years of age:do not use

Directions(1000 mL)

■ adults and children 6 years of age and older:vigorously swish 20 milliliters (4 teaspoonfuls) of rinse between your teeth twice a day for 30 seconds and then spit out. Do not swallow the rinse. Do not rinse with water. Do not drink from the bottle.

■ children 6 years to under 12 years of age:supervise use

■ children under 6 years of age:do not use

Other information

■ this product is not intended to replace brushing or flossing

■ may cause staining

■ do not store above 25°C (77°F)

Inactive ingredients

water, glycerin, poloxamer 407, flavor, benzoic acid, sodium benzoate, sucralose, zinc lactate, sodium saccharin, green 3, yellow 6, cinnamal

Questions or comments?

1-866-844-2797

Additional information

parodontax

ACTIVE GUMHEALTH

BREATH FRESHENER

With Breath Cleanse Technology that is designed to kill bacteria that cause bad breath.

ALWAYS FOLLOW THE LABEL
Do not use if printed safety seal around cap is broken or missing.

*Kills plaque bacteria associated with gingivitis in a laboratory test

Distributed by: Haleon,Warren, NJ 07059

Trademarks owned or licensed by Haleon.

©2025 Haleon or licensor.

Proudly made in the USA with US & globally sourced ingredients. Active made in India.

BOTTLE
RECYCLE

CAP
CHECK LOCALLY†

†Recycling facilities for this product may not exist in your area. Cap film not recyclable.

Principal Display Panel

NEW LOOK

HALEON

DENTIST RECOMMENDED

parodontax

CPC ANTIGINGIVITIS/ANTIPLAQUE MOUTHRINSE

ACTIVE GUMHEALTH

DAILY MOUTHWASH

HELPS PREVENT BLEEDING GUMS

& BAD BREATH BACTERIA

BREATH CLEANSE TECHNOLOGY

BREATH FRESHENER

KILLS 99.9%
PLAQUE BACTERIA*

0% ALCOHOL

NET WT 16.9 FL OZ (500 mL)

216841
L0021380FC